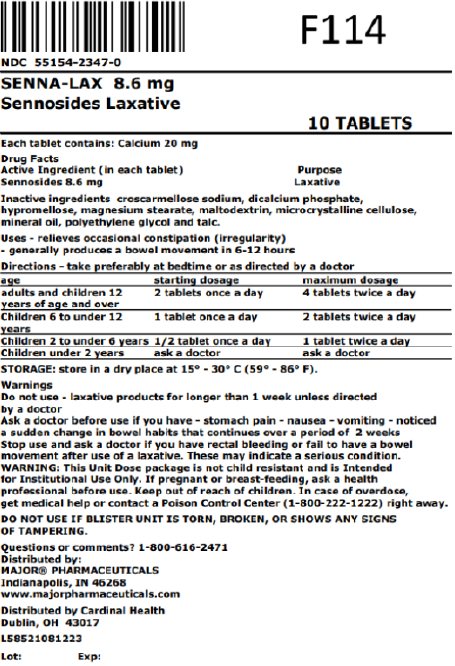 DRUG LABEL: Sennosides
NDC: 55154-2347 | Form: TABLET, FILM COATED
Manufacturer: Cardinal Health 107, LLC
Category: otc | Type: HUMAN OTC DRUG LABEL
Date: 20251028

ACTIVE INGREDIENTS: SENNOSIDES 8.6 mg/1 1
INACTIVE INGREDIENTS: CROSCARMELLOSE SODIUM; DIBASIC CALCIUM PHOSPHATE DIHYDRATE; HYPROMELLOSE, UNSPECIFIED; MAGNESIUM STEARATE; MALTODEXTRIN; MICROCRYSTALLINE CELLULOSE; LIGHT MINERAL OIL; POLYETHYLENE GLYCOL 400; TALC

1122W-Major

Drug Facts

Active ingredient (in each tablet)
Sennosides 8.6 mg

Purpose
Laxative

Uses

 relieves occasional constipation (irregularity)
 generally produces a bowel movement in 6-12 hours

Warnings

.

Do not use

 laxative products for longer than 1 week unless directed by a doctor

Ask a doctor before use if you have

 stomach pain

 nausea

 vomiting

 noticed a sudden change in bowel habits that continues over a period of 2 weeks

Stop use and ask a doctor if

you have rectal bleeding or fail to have a bowel movement after use of a laxative. These may indicate a serious condition.

If pregnant or breast-feeding,

ask a health professional before use.

Keep out of reach of children.

In case of overdose, get medical help or contact a Poison Control Center (1-800-222-1222) right away.

Directions

 take preferably at bedtime or as directed by a doctor

age | starting dosage | maximum dosage
adults and children 12 years of age and over | 2 tablets once a day | 4 tablets twice a day
children 6 to under 12 years | 1 tablet once a day | 2 tablets twice a day
children 2 to under 6 years | 1/2 tablet once a day | 1 tablet twice a day
children under 2 years | ask a doctor | ask a doctor

Other information

 each tablet contains: calcium 20 mg.
 store in a dry place at 15° – 30°C (59° – 86°F).

Inactive Ingredients

croscarmellose sodium, dicalcium phosphate, hypromellose, magnesium stearate, maltodextrin, microcrystalline cellulose, mineral oil, polyethylene glycol, talc.

Questions or comments?

1-800-616-2471

.

TAMPER EVIDENT: DO NOT USE IF PRINTED SAFETY SEAL UNDER CAP IS BROKEN OR MISSING.

Distributed by:
MAJOR® PHARMACEUTICALS
Indianapolis, IN 46268

*This product is not manufactured or distributed by Avrio Health L.P., owner of the registered trademark Senokot®.

Overbagged with 10 tablets per bag, NDC 55154-2347-0

WARNING: This Unit Dose package is not child resistant and is Intended for Institutional Use Only. Keep this and all drugs out of the reach of children.

Rev. 05.22 | M-29 | Re-order No. 701313 | R51255

Distributed By:

Cardinal Health

Dublin, OH 43017

L58521081223

Principal Display Panel

NDC 55154-2347-0

SENNA-LAX 8.6 mg

Sennosides Laxative

10 TABLETS